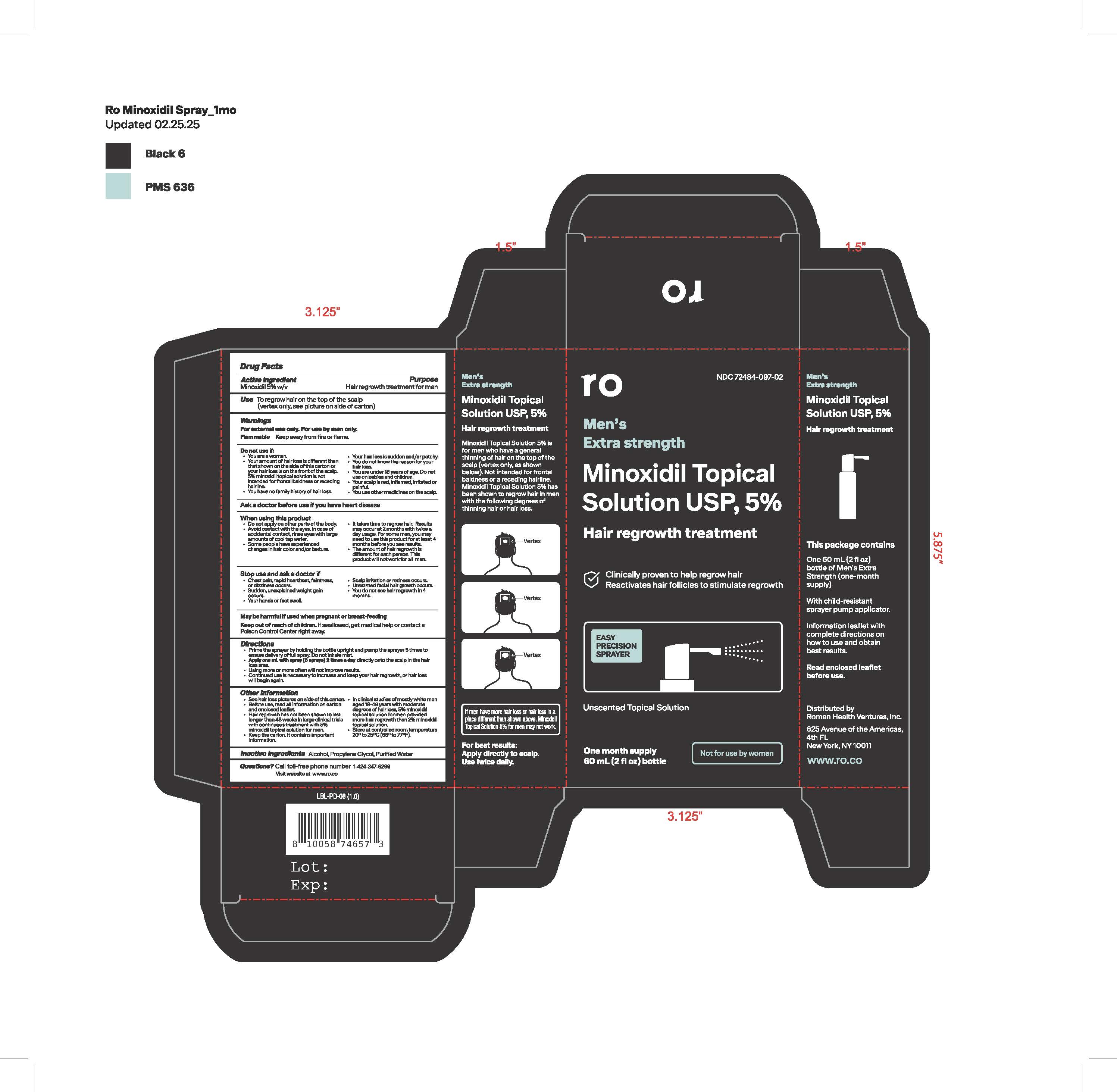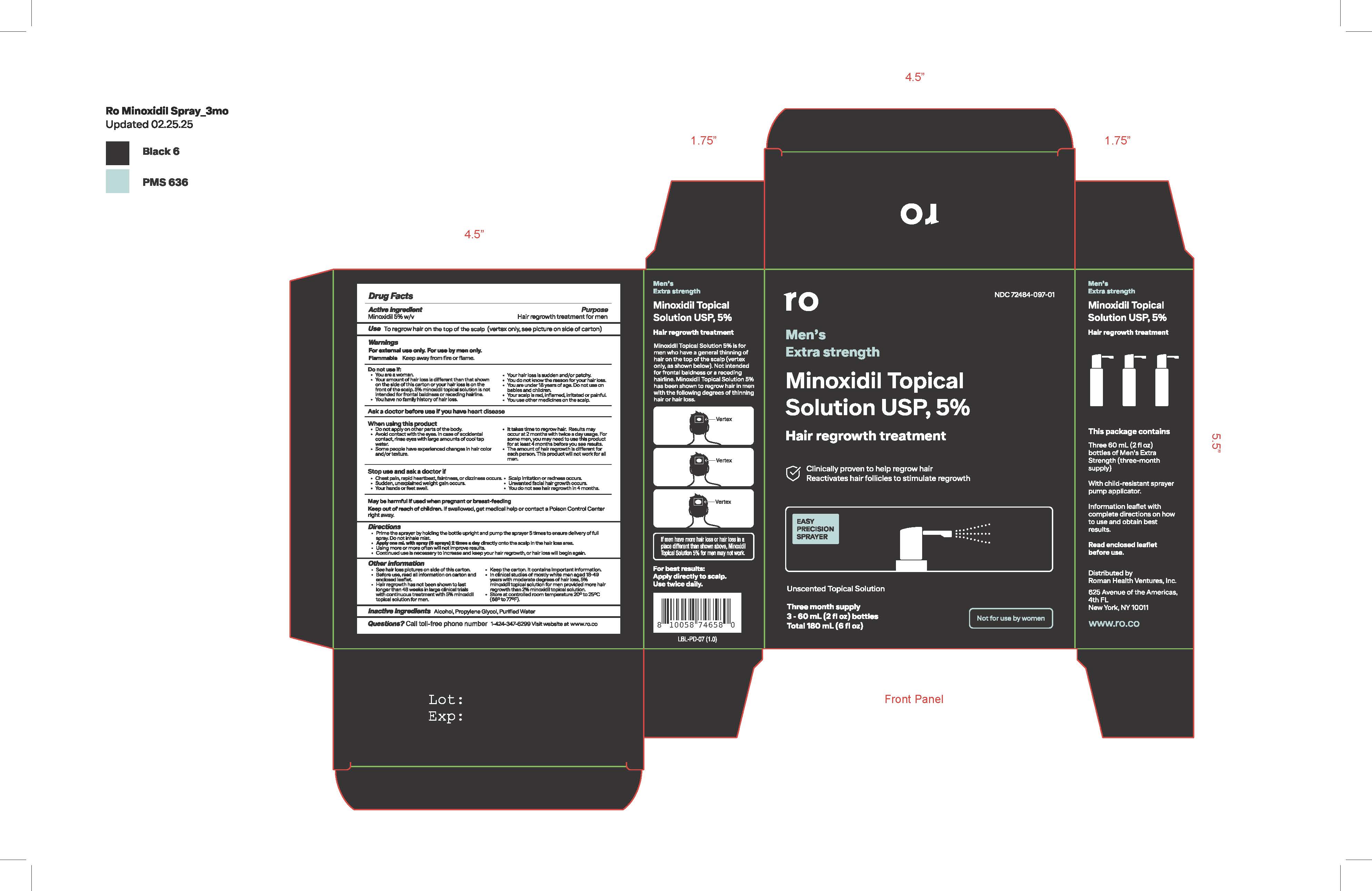 DRUG LABEL: Minoxidil
NDC: 72484-097 | Form: SPRAY
Manufacturer: Roman Health Ventures Inc.
Category: otc | Type: HUMAN OTC DRUG LABEL
Date: 20250130

ACTIVE INGREDIENTS: MINOXIDIL 5 g/100 mL
INACTIVE INGREDIENTS: ALCOHOL; WATER; PROPYLENE GLYCOL

Minoxidil Spray

Drug Facts

ACTIVE INGREDIENT

1 Bottle Carton

Active Ingredient

Minoxidil, USP 5% w/v

3 Bottle Carton

Active Ingredient

Minoxidil 5% w/v

PURPOSE

1 Bottle Carton

Purpose

Hair regrowth treatment for men

3 Bottle Carton

Purpose

Hair regrowth treatment

INDICATIONS AND USAGE

1 Bottle Carton

Use to regrow hair on the scalp (vertex only, see picture on side of carton)

3 Bottle Carton

Use to regrow hair on the scalp (vertex only, see picture on side of carton)

Warnings

For external use only. For use by men only.

Flammable: Keep away from fire or flame

Directions

Prime the sprayer by holding the bottle the bottle upright and pump the sprayer 5 times to ensure delivery of full spray. Do not inhale mist

Apply one mL with spray (6 sprays) 2 times a day directly onto the scalp in the hair loss area

Using more or more often will not improve restuls

Continued use is necessary to increase and keep your hair regrowth, or hair loss will begind again.

Other information

See hair loss pictures on side of this carton

Before use, read all information on carton and enclosed leaflet

Hair regrowth has not been shown to last longer than 48 weeks in large clinical trials with continuous treatment with 5% minoxidil topical solution for men

Keep the carton. It contains important information.

In clinical studies of mostly white men aged 18-45 years with moderate degrees of hairloss, 5% minoxidil topical solution for men provided more hair regrowth than 2% minoxidil topical solution

Store at controlled room temperature 20 to 25C (68 to 77F)

Inactive ingredients Alcohol, propylene glycol, purified water

QUESTIONS

Questions? 1-424-347-6299 Visit website at ro.co

Distributed by

Roman Health Ventures, Inc.

116 W. 23rd Street, 4th Floor

New York, NY 10011

www.ro.co

NOT FOR USE BY WOMEN:

May grow facial hair. May be harmful if used during pregnancy or breast-feeding

Minoxidil 5% Topical Solution, USP

Minoxidil 5% Topical Solution

is for men who have a general

thinning of hair on the top of

the scalp vertex only, as

shown below. Not intended

for frontabl baldness or a

receding hairline. Minoxidil

Topical Solution 5% has been

shown to regrow hair in men

with the following degrees of

thinning hair or hairloss.

If men have more hair loss or hair loss in

a place different than showing above, Minoxidil

Topical Solution 5% for men may not work.

For best results:

Apply direclty to scalp. Use twice daily.

Three Bottle Package

NDC xxxxx-xxx-xx

roman

HAIR

REGROWTH

TREATMENT

5% Minoxidil Topical Solution, USP

Extra Strength formula for men

Clinically proven to help regrow hair

Reactivates hair follicles to stimulate growth

Easy precision sprayer

Unscented topical solution

Three month supply

3- 60 mL (2 fl oz) bottles

Total 180 mL (6 fl oz)

Not for use by women

Single Bottle Package

NDC XXXXX-XXX-XX

roman

Hair Regrowth Treatment

5% Minoxidil Topical Solution, USP

Extra Strength formula for men

Clinically proven to help regrow hair

Reactivates hair follicales to stimulate regrowth

Easy precision sprayer

Unscented topical solution

One month supply

1 - 60 mL (2 fl oz) bottle

Not for use by women.